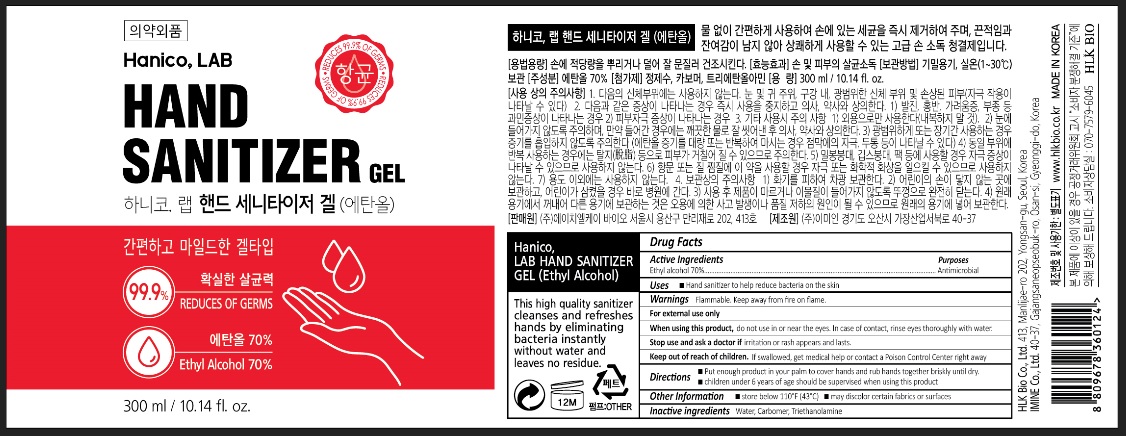 DRUG LABEL: Hanico LAB HAND SANITIZER gel
NDC: 78552-001 | Form: GEL
Manufacturer: HLK Bio Co., Ltd.
Category: otc | Type: HUMAN OTC DRUG LABEL
Date: 20200605

ACTIVE INGREDIENTS: ALCOHOL 0.7 g/1 mL
INACTIVE INGREDIENTS: WATER; CARBOMER HOMOPOLYMER, UNSPECIFIED TYPE; TROLAMINE

78552-001_Hanico. LAB HAND SANITIZER GEL

Active ingredient

Ethyl alcohol 70%

Purpose

Antimicrobial

Use

- Hand sanitizer to help reduce bacteria on the skin

Warnings

Flammable. Keep away from fire or flame.

For external use only

When using this product do not use in or near the eyes. In case of contact, rinse eyes thoroughly with water.

Stop use and ask a doctor if irritation or rash appears and lasts

Keep out of reach of children. If swallowed, get medical help or contact a Poison Control Center right away.

Directions

- Put nough produt in your palm to cover hands and rub hands together briskly until dry.
- Children under 6 years of age should be supervised when using this product

Other information

- Store below 110°F (43°C)
- May discolor certain fabrics or surfaces

Inactive ingredients

Water, Carbomer, Triethanolamine